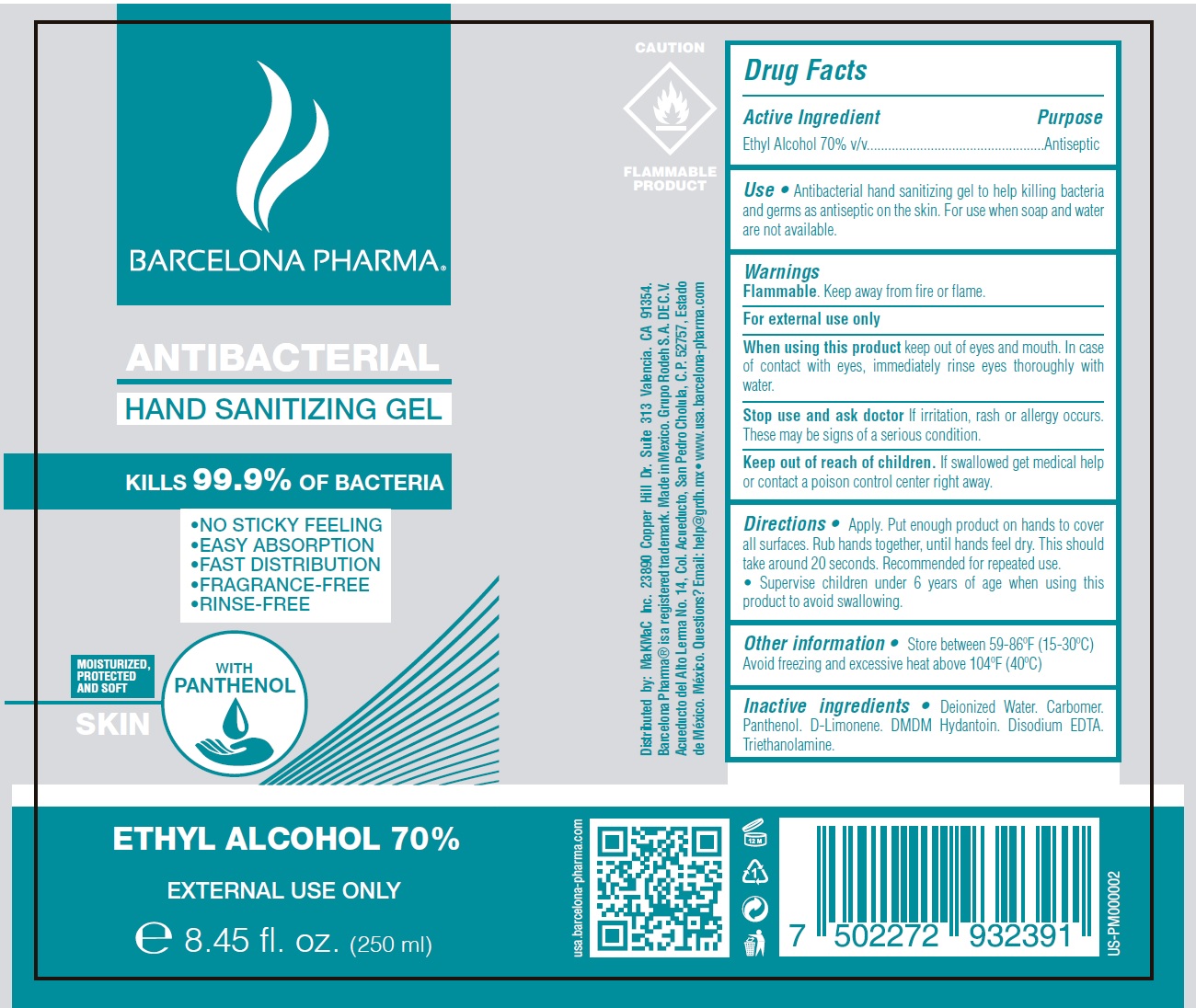 DRUG LABEL: ANTIBACTERIAL HAND SANITIZING
NDC: 78080-001 | Form: GEL
Manufacturer: MaKMaC Inc
Category: otc | Type: HUMAN OTC DRUG LABEL
Date: 20200519

ACTIVE INGREDIENTS: ALCOHOL 0.7 mL/1 mL
INACTIVE INGREDIENTS: WATER; CARBOMER HOMOPOLYMER, UNSPECIFIED TYPE; PANTHENOL; LIMONENE, (+)-; DMDM HYDANTOIN; EDETATE DISODIUM ANHYDROUS; TROLAMINE

ANTIBACTERIAL HAND SANITIZING GEL

Active Ingredient

Ethyl Alcohol 70% v/v

Purpose

Antiseptic

Use

- Antibacterial hand sanitizing gel to help killing bacteria and germs as antiseptic on the skin. For use when soap and water are not available.

Warnings

Flammable. Keep away from fire or flame.

For external use only

When using this product

keep out of eyes and mouth. In case of contact with eyes, immediately rinse eyes thoroughly with water

Stop use and ask doctor

If irritation, rash or allergy occurs. These may be signs of a serious condition

Keep out of reach of children.

If swallowed get medical help or contact a poison control center right away

Directions

- Apply. Put enough product on hands to cover all surfaces. Rub hands together, until hands feel dry. This should take around 20 seconds. recommended for repeated use.
- Supervise children under 6 years of age when using this product to avoid swallowing.

Other information

• Store between 59-86ºF (15-30ºC) avoid freezing and excessive heat above 104ºF (40ºC)

Inactive ingredients

• Deionized Water. Carbomer. Panthenol. D-Limonene. DMDM Hydantoin. Disodium EDTA Triethanolamine.